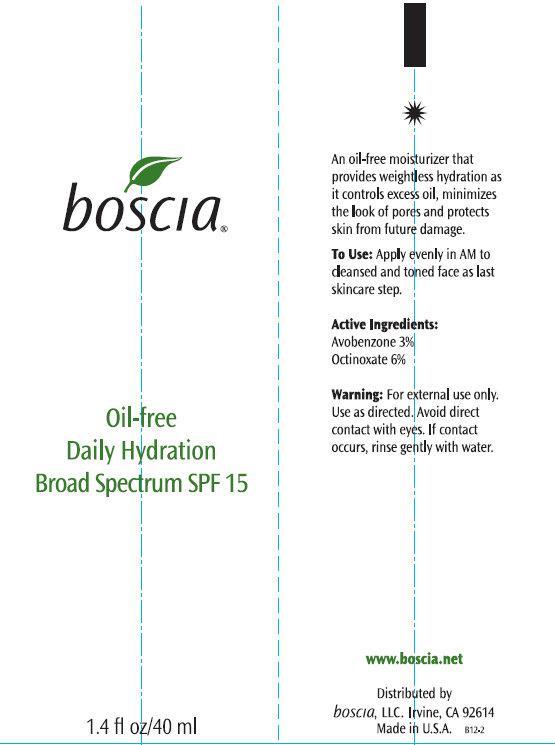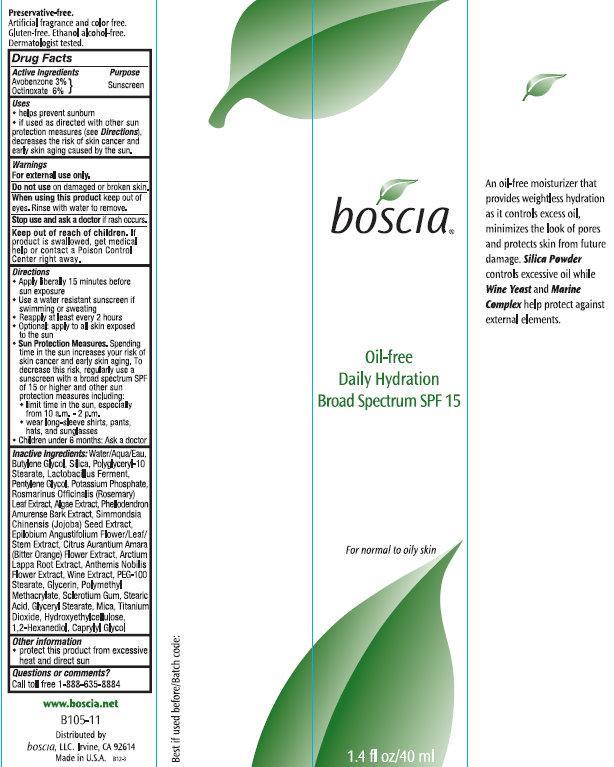 DRUG LABEL: Boscia Daily Hydration SPF 15 Broad Spectrum For Normal To Oily Skin
NDC: 76151-106 | Form: CREAM
Manufacturer: Boscia LLC
Category: otc | Type: HUMAN OTC DRUG LABEL
Date: 20231212

ACTIVE INGREDIENTS: AVOBENZONE 30 mg/1 mL; OCTINOXATE 60 mg/1 mL
INACTIVE INGREDIENTS: 1,2-HEXANEDIOL; CAPRYLYL GLYCOL; WATER; BUTYLENE GLYCOL; SILICON DIOXIDE; POLYGLYCERYL-10 STEARATE; PENTYLENE GLYCOL; POTASSIUM PHOSPHATE, UNSPECIFIED FORM; ROSEMARY; PHELLODENDRON AMURENSE BARK; SIMMONDSIA CHINENSIS SEED; EPILOBIUM ANGUSTIFOLIUM FLOWERING TOP; CITRUS AURANTIUM FLOWER; ARCTIUM LAPPA ROOT; CHAMAEMELUM NOBILE FLOWER; PEG-100 STEARATE; GLYCERIN; STEARIC ACID; GLYCERYL MONOSTEARATE; MICA; TITANIUM DIOXIDE

Boscia Oil-Free Daily Hydration SPF 15 Broad Spectrum For Normal To Oily Skin

Active Ingredients

Avobenzone 3 % Octinoxate 6%

Purpose

Sunscreen

Uses

- helps prevent sunburn
- if used as directed with other sun protection measures (see), decreases the risk of skin cancer and early skin aging caused by the sun. Directions

Warnings

For external use only.

Do not use

on damaged or broken skin.

When using this product

keep out of eyes. Rinse with water to remove.

Stop use and ask a doctor

if rash occurs.

Keep out of reach of children.

If product is swallowed, get medical help or contact a Poison Control Center right away.

Directions

- Apply liberally 15 minutes before sun exposure.
- Use a water resistant sunscreen if swimming or sweating
- Reapply at least every 2 hours
- Optional: apply to all skin exposed to the sun
- Spending time in the sun increases your risk of skin cancer and early skin aging. To decrease this risk, regularly use a sunscreen with a broad spectrum SPF of 15 or higher and other sun protection measures including: Sun Protection Measures.
- limit time in the sun, especially from 10 a.m. - 2 p.m.
- wear long-sleeve shirts, pants, hats, and sunglasses.
- Children under 6 months: Ask a doctor.

Inactive Ingredients:

Water/Aqua/Eau, Butylene Glycol, Silica, Polyglyceryl-10 Stearate, Lactobacillus Ferment, Pentylene Glycol, Potassium Phosphate, Rosmarinus Officinalis (Rosemary) Leaf Extract, Algae Extract, Phellodendron Amurense Bark Extract, Simmondsia Chinensis (Jojoba) Seed Extract, Epilobium Angustifolium Flower/Leaf/Stem Extract, Citrus Aurantium Amara (Bitter Orange) Flower Extract, Arctium Lappa Root Extract, Anthemis Nobilis Flower Extract, Wine Extract, PEG-100 Stearate, Glycerin, Polymethyl Methacrylate, Sclerotilum Gum, Stearic Acid, Glyceryl Stearate, Mica, Titanium Dioxide, Hydroxyethylcellulose, 1,2-Hexanediol, Caprylyl Glycol

Other information

- protect this product from excessive heat and direct sun

Questions or comments?

Call toll free 1-888-635-8884

An oil-free moisturizer that provides weightless hydration as it controls excess oil, minimizes the look of pores and protects skin from future damage. controls excessive oil while and help protect against external elements. Silica Powder Wine Yeast Marine Complex

Artificial fragrance and color free. Gluten-free. Ethanol alcohol-free. Dermatologist tested. Preservative-free.

PACKAGE LABEL

boscia Oil-free Daily Hydration Broad Spectrum SPF 15 1.4 fl oz/40 ml For normal to oily skin